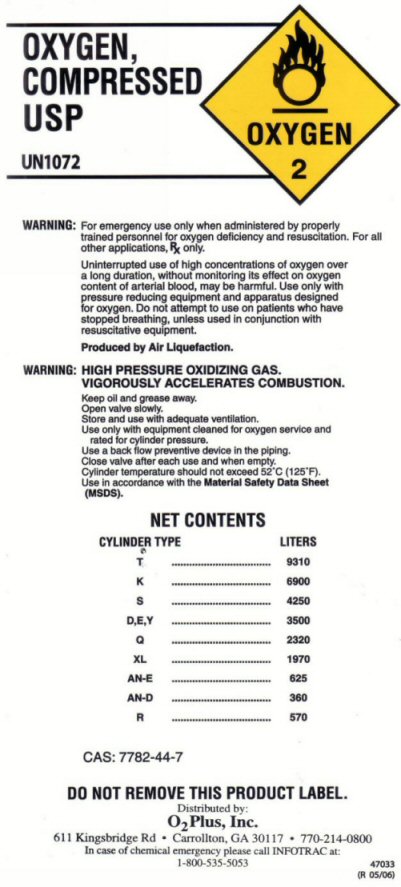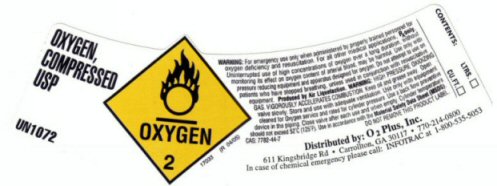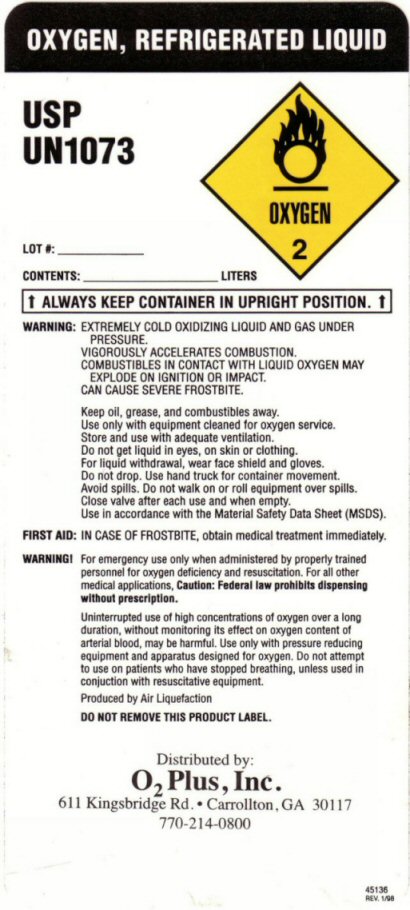 DRUG LABEL: OXYGEN
NDC: 64464-001 | Form: GAS
Manufacturer: O2 Plus, Inc
Category: prescription | Type: HUMAN PRESCRIPTION DRUG LABEL
Date: 20251024

ACTIVE INGREDIENTS: OXYGEN 99 L/100 L

OXYGEN COMPRESSED LABEL

WARNING: FOR EMERGENCY USE ONLY WHEN ADMINISTERED BY PROPERLY TRAINED PERSONNEL FOR OXYGEN DEFICIENCY AND RESUSCITATION. FOR ALL OTHER MEDICAL APPLICATIONS Rx ONLY. CAUTION: FEDERAL LAW PROHIBITS DISPENSING WITHOUT PRESCRIPTION. UNINTERRUPTED USE OF HIGH CONCENTRATIONS OF OXYGEN OVER A LONG DURATION WITHOUT MONITORING ITS EFFECT ON OXYGEN CONTENT OF ARTERIAL BLOOD MAY BE HARMFUL. USE ONLY WITH PRESSURE REDUCING EQUIPMENT AND APPARATUS DESIGNED FOR OXYGEN. DO NOT ATTEMPT TO USE ON PATIENTS WHO HAVE STOPPED BREATHING UNLESS USED IN CONJUNCTION WITH RESUSCITATIVE EQUIPMENT. PRODUCED BY AIR LIQUEFACTION. DO NOT REMOVE THIS PRODUCT LABEL. WARNING: HIGH PRESSURE GAS VIGOROUSLY ACCELERATES COMBUSTION. KEEP OIL AND GREASE AWAY. OPEN VALVE SLOWLY. STORE AND USE WITH ADEQUATE VENTILATION. USE ONLY WITH EQUIPMENT CLEANED FOR OXYGEN SERVICE AND RATED FOR CYLINDER PRESSURE. USE A BACK FLOW PREVENTATIVE DEVICE IN THE PIPING. CLOSE VALVE AFTER EACH USE AND WHEN EMPTY. CYLINDER TEMPERATURE SHOULD NOT EXCEED 52 C (125 F) USE IN ACCORDANCE WITH THE MATERIAL SAFETY DATA SHEET (MSDS)

NET CONTENTS

CYLINDER TYPE LITERS

T 9310

K 6900

S 4250

D,E,Y 3500

Q 2320

XL 1970

AN-E 625

AN-D 360

R 570

CAS 7782-44-7 IN CASE OF CHEMICAL EMERGENCY PLEASE CALL INFOTRAC AT 1-800-535-5053

OXYGEN REFRIGERATED LIQUID LABEL

OXYGEN REFRIGERATED LIQUID USP UN1073 OXYGEN-2 LOT#_____ CONTENTS_____LITERS ALWAYS KEEP CONTAINER IN UPRIGHT POSITION WARNING: EXTREMELY COLD OXIDIZING LIQUID AND GAS UNDER PRESSURE. VIGOROUSLY ACCELERATES COMBUSTION COMBUSTIBLES IN CONTACT WITH LIQUID OXYGEN MAY EXPLODE ON IGNITION OR IMPACT CAN CAUSE SEVERE FROSTBITE KEEP OIL, GREASE AND COMBUSTIBLES AWAY USE ONLY WITH EQUIPMENT CLEANED FOR OXYGEN SERVICE. STORE AND USE WITH ADEQUATE VENTILATION. DO NOT GET LIQUID LIN EYES, ON SKIN OR CLOTHING. FOR LIQUID WITHDRAWAL WEAR FACE SHIELD AND GLOVES. DO NOT DROP. USE HAND TRUCK FOR CONTAINER MOVEMENT. AVOID SPILLS. DO NOT WALK ON OR ROLL EQUIPMENT OVER SPILLS. CLOSE VALVE AFTER EACH USE AND WHEN EMPTY. USE IN ACCORDANCE WITH MATERIAL SAFETY DATA SHEET (MSDS). FIRST AID: IN CASE OF FROSTBITE OBTAIN MEDICAL TREATMENT IMMEDIATELY. WARNING: FOR EMERGENCY USE ONLY WHEN ADMINISTERED BY PROPERLY TRAINED PERSONNEL FOR OXYGEN DEFICIENCY AND RESUSCITATION. FOR ALL OTHER MEDICAL APPLICATIONS Rx ONLY. CAUTION: FEDERAL LAW PROHIBITS DISPENSING WITHOUT PRESCRIPTION. UNINTERRUPTED USE OF HIGH CONCENTRATIONS OF OXYGEN OVER A LONG DURATION WITHOUT MONITORING ITS EFFECT ON OXYGEN CONTENT OF ARTERIAL BLOOD MAY BE HARMFUL. USE ONLY WITH PRESSURE REDUCING EQUIPMENT AND APPARATUS DESIGNED FOR OXYGEN. DO NOT ATTEMPT TO USE ON PATIENTS WHO HAVE STOPPED BREATHING UNLESS USED IN CONJUNCTION WITH RESUSCITATIVE EQUIPMENT. PRODUCED BY AIR LIQUEFACTION. DO NOT REMOVE THIS PRODUCT LABEL.

res